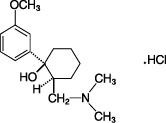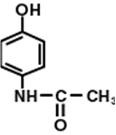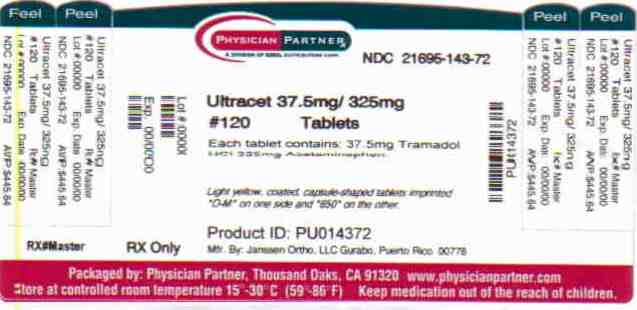 DRUG LABEL: ULTRACET
NDC: 21695-143 | Form: TABLET
Manufacturer: Rebel Distributors Corp
Category: prescription | Type: HUMAN PRESCRIPTION DRUG LABEL
Date: 20101201

ACTIVE INGREDIENTS: tramadol hydrochloride 37.5 mg/1 1; acetaminophen 325 mg/1 1
INACTIVE INGREDIENTS: POWDERED CELLULOSE; STARCH, CORN; SODIUM STARCH GLYCOLATE TYPE A POTATO; magnesium stearate; HYPROMELLOSES; POLYETHYLENE GLYCOL; POLYSORBATE 80; titanium dioxide; FERRIC OXIDE RED; CARNAUBA WAX

ULTRACET® (TRAMADOL HYDROCHLORIDE/ACETAMINOPHEN) TABLETS

DESCRIPTION

ULTRACET® (tramadol hydrochloride/acetaminophen) Tablets combines two analgesics, tramadol 37.5 mg and acetaminophen 325 mg.

The chemical name for tramadol hydrochloride is (±)cis-2-[(dimethylamino)methyl]-1-(3-methoxyphenyl) cyclohexanol hydrochloride. Its structural formula is:

The molecular weight of tramadol hydrochloride is 299.84. Tramadol hydrochloride is a white, bitter, crystalline and odorless powder.

The chemical name for acetaminophen is N-acetyl-p-aminophenol. Its structural formula is:

The molecular weight of acetaminophen is 151.17. Acetaminophen is an analgesic and antipyretic agent which occurs as a white, odorless, crystalline powder, possessing a slightly bitter taste.

ULTRACET® tablets contain 37.5 mg tramadol hydrochloride and 325 mg acetaminophen and are light yellow in color. Inactive ingredients in the tablet are powdered cellulose, pregelatinized corn starch, sodium starch glycolate, corn starch, magnesium stearate, hypromellose, polyethylene glycol, polysorbate 80, titanium dioxide, iron oxide, and carnauba wax.

CLINICAL PHARMACOLOGY

The following information is based on studies of tramadol alone or acetaminophen alone, except where otherwise noted:

Pharmacodynamics

Tramadol is a centrally acting synthetic opioid analgesic. Although its mode of action is not completely understood, from animal tests, at least two complementary mechanisms appear applicable: binding of parent and M1 metabolite to µ-opioid receptors and weak inhibition of reuptake of norepinephrine and serotonin.

Opioid activity is due to both low affinity binding of the parent compound and higher affinity binding of the O-demethylated metabolite M1 to µ-opioid receptors. In animal models, M1 is up to 6 times more potent than tramadol in producing analgesia and 200 times more potent in µ-opioid binding. Tramadol-induced analgesia is only partially antagonized by the opiate antagonist naloxone in several animal tests. The relative contribution of both tramadol and M1 to human analgesia is dependent upon the plasma concentrations of each compound (see CLINICAL PHARMACOLOGY, Pharmacokinetics).

Tramadol has been shown to inhibit reuptake of norepinephrine and serotonin in vitro, as have some other opioid analgesics. These mechanisms may contribute independently to the overall analgesic profile of tramadol.

Apart from analgesia, tramadol administration may produce a constellation of symptoms (including dizziness, somnolence, nausea, constipation, sweating and pruritus) similar to that of other opioids.

Acetaminophen

Acetaminophen is a non-opiate, non-salicylate analgesic.

Pharmacokinetics

Tramadol is administered as a racemate and both the [-] and [+] forms of both tramadol and M1 are detected in the circulation. The pharmacokinetics of plasma tramadol and acetaminophen following oral administration of one ULTRACET® tablet are shown in Table 1. Tramadol has a slower absorption and longer half-life when compared to acetaminophen.

Table 1: Summary of Mean (±SD) Pharmacokinetic Parameters of the (+)- and (-) Enantiomers of Tramadol and M1 and Acetaminophen Following A Single Oral Dose Of One Tramadol/Acetaminophen Combination Tablet (37.5 mg/325 mg) in Volunteers
Parameter [For acetaminophen, Cmax was measured asµg/mL.] | (+)-Tramadol |  | (-)-Tramadol |  | (+)-M1 |  | (-)-M1 |  | acetaminophen
Cmax (ng/mL) | 64.3 | (9.3) | 55.5 | (8.1) | 10.9 | (5.7) | 12.8 | (4.2) | 4.2 | (0.8)
tmax (h) | 1.8 | (0.6) | 1.8 | (0.7) | 2.1 | (0.7) | 2.2 | (0.7) | 0.9 | (0.7)
CL/F (mL/min) | 588 | (226) | 736 | (244) | - | - | - | - | 365 | (84)
t1/2 (h) | 5.1 | (1.4) | 4.7 | (1.2) | 7.8 | (3.0) | 6.2 | (1.6) | 2.5 | (0.6)

A single dose pharmacokinetic study of ULTRACET® in volunteers showed no drug interactions between tramadol and acetaminophen. Upon multiple oral dosing to steady state, however, the bioavailability of tramadol and metabolite M1 was lower for the combination tablets compared to tramadol administered alone. The decrease in AUC was 14% for (+)-tramadol, 10.4% for (-)-tramadol, 11.9% for (+)-M1 and 24.2% for (-)-M1. The cause of this reduced bioavailability is not clear. Following single or multiple dose administration of ULTRACET®, no significant change in acetaminophen pharmacokinetics was observed when compared to acetaminophen given alone.

Absorption

The absolute bioavailability of tramadol from ULTRACET® tablets has not been determined. Tramadol hydrochloride has a mean absolute bioavailability of approximately 75% following administration of a single 100 mg oral dose of ULTRAM® tablets. The mean peak plasma concentration of racemic tramadol and M1 after administration of two ULTRACET® tablets occurs at approximately two and three hours, respectively, post-dose.

Peak plasma concentrations of acetaminophen occur within one hour and are not affected by co-administration with tramadol. Oral absorption of acetaminophen following administration of ULTRACET® occurs primarily in the small intestine.

Food Effects

When ULTRACET® was administered with food, the time to peak plasma concentration was delayed for approximately 35 minutes for tramadol and almost one hour for acetaminophen. However, peak plasma concentration or the extent of absorption of either tramadol or acetaminophen were not affected. The clinical significance of this difference is unknown.

Distribution

The volume of distribution of tramadol was 2.6 and 2.9 L/kg in male and female subjects, respectively, following a 100 mg intravenous dose. The binding of tramadol to human plasma proteins is approximately 20% and binding also appears to be independent of concentration up to 10 µg/mL. Saturation of plasma protein binding occurs only at concentrations outside the clinically relevant range.

Acetaminophen appears to be widely distributed throughout most body tissues except fat. Its apparent volume of distribution is about 0.9 L/kg. A relative small portion (~20%) of acetaminophen is bound to plasma protein.

Metabolism

Following oral administration, tramadol is extensively metabolized by a number of pathways, including CYP2D6 and CYP3A4, as well as by conjugation of parent and metabolites. Approximately 30% of the dose is excreted in the urine as unchanged drug, whereas 60% of the dose is excreted as metabolites. The major metabolic pathways appear to be N - and O- demethylation and glucuronidation or sulfation in the liver. Metabolite M1 (O -desmethyltramadol) is pharmacologically active in animal models. Formation of M1 is dependent on CYP2D6 and as such is subject to inhibition, which may affect the therapeutic response (see PRECAUTIONS, Drug Interactions).

Approximately 7% of the population has reduced activity of the CYP2D6 isoenzyme of cytochrome P450. These individuals are "poor metabolizers" of debrisoquine, dextromethorphan, tricyclic antidepressants, among other drugs. Based on a population PK analysis of Phase 1 studies in healthy subjects, concentrations of tramadol were approximately 20% higher in "poor metabolizers" versus "extensive metabolizers", while M1 concentrations were 40% lower. In vitro drug interaction studies in human liver microsomes indicates that inhibitors of CYP2D6 such as fluoxetine and its metabolite norfluoxetine, amitriptyline and quinidine inhibit the metabolism of tramadol to various degrees. The full pharmacological impact of these alterations in terms of either efficacy or safety is unknown. Concomitant use of SEROTONIN re-uptake INHIBITORS and MAO INHIBITORS may enhance the risk of adverse events, including seizure (see WARNINGS) and serotonin syndrome.

Acetaminophen is primarily metabolized in the liver by first-order kinetics and involves three principal separate pathways:

- a)conjugation with glucuronide;
- b)conjugation with sulfate; and
- c)oxidation via the cytochrome, P450-dependent, mixed-function oxidase enzyme pathway to form a reactive intermediate metabolite, which conjugates with glutathione and is then further metabolized to form cysteine and mercapturic acid conjugates. The principal cytochrome P450 isoenzyme involved appears to be CYP2E1, with CYP1A2 and CYP3A4 as additional pathways.

In adults, the majority of acetaminophen is conjugated with glucuronic acid and, to a lesser extent, with sulfate. These glucuronide-, sulfate-, and glutathione-derived metabolites lack biologic activity. In premature infants, newborns, and young infants, the sulfate conjugate predominates.

Elimination

Tramadol is eliminated primarily through metabolism by the liver and the metabolites are eliminated primarily by the kidneys. The plasma elimination half-lives of racemic tramadol and M1 are approximately 5–6 and 7 hours, respectively, after administration of ULTRACET®. The apparent plasma elimination half-life of racemic tramadol increased to 7–9 hours upon multiple dosing of ULTRACET®.

The half-life of acetaminophen is about 2 to 3 hours in adults. It is somewhat shorter in children and somewhat longer in neonates and in cirrhotic patients. Acetaminophen is eliminated from the body primarily by formation of glucuronide and sulfate conjugates in a dose-dependent manner. Less than 9% of acetaminophen is excreted unchanged in the urine.

Special Populations

Renal

The pharmacokinetics of ULTRACET® in patients with renal impairment has not been studied. Based on studies using tramadol alone, excretion of tramadol and metabolite M1 is reduced in patients with creatinine clearance of less than 30 mL/min, adjustment of dosing regimen in this patient population is recommended (see DOSAGE AND ADMINISTRATION). The total amount of tramadol and M1 removed during a 4-hour dialysis period is less than 7% of the administered dose based on studies using tramadol alone.

Hepatic

The pharmacokinetics and tolerability of ULTRACET® in patients with impaired hepatic function has not been studied. Since tramadol and acetaminophen are both extensively metabolized by the liver, the use of ULTRACET® in patients with hepatic impairment is not recommended (see PRECAUTIONS and DOSAGE AND ADMINISTRATION).

Geriatric

A population pharmacokinetic analysis of data obtained from a clinical trial in patients with chronic pain treated with ULTRACET® which included 55 patients between 65 and 75 years of age and 19 patients over 75 years of age, showed no significant changes in pharmacokinetics of tramadol and acetaminophen in elderly patients with normal renal and hepatic function (see PRECAUTIONS, Geriatric Use).

Gender

Tramadol clearance was 20% higher in female subjects compared to males on four phase I studies of ULTRACET® in 50 male and 34 female healthy subjects. The clinical significance of this difference is unknown.

Pediatric

Pharmacokinetics of ULTRACET® tablets has not been studied in pediatric patients below 16 years of age.

CLINICAL STUDIES

Single Dose Studies for Treatment of Acute Pain

In pivotal single-dose studies in acute pain, two tablets of ULTRACET® administered to patients with pain following oral surgical procedures provided greater relief than placebo or either of the individual components given at the same dose. The onset of pain relief after ULTRACET® was faster than tramadol alone. Onset of analgesia occurred in less than one hour. The duration of pain relief after ULTRACET® was longer than acetaminophen alone. Analgesia was generally comparable to that of the comparator, ibuprofen.

INDICATIONS AND USAGE

ULTRACET® is indicated for the short-term (five days or less) management of acute pain.

CONTRAINDICATIONS

ULTRACET® should not be administered to patients who have previously demonstrated hypersensitivity to tramadol, acetaminophen, any other component of this product or opioids. ULTRACET® is contraindicated in any situation where opioids are contraindicated, including acute intoxication with any of the following: alcohol, hypnotics, narcotics, centrally acting analgesics, opioids or psychotropic drugs. ULTRACET® may worsen central nervous system and respiratory depression in these patients.

WARNINGS

Seizure Risk

Seizures have been reported in patients receiving tramadol within the recommended dosage range. Spontaneous post-marketing reports indicate that seizure risk is increased with doses of tramadol above the recommended range. Concomitant use of tramadol increases the seizure risk in patients taking:

- Selective serotonin reuptake inhibitors (SSRI antidepressants or anorectics),
- Tricyclic antidepressants (TCAs), and other tricyclic compounds (e.g., cyclobenzaprine, promethazine, etc.), or
- Other opioids.

Administration of tramadol may enhance the seizure risk in patients taking:

- MAO inhibitors (see also WARNINGS, Use with MAO Inhibitors and Serotonin Re-uptake Inhibitors),
- Neuroleptics, or
- Other drugs that reduce the seizure threshold.

Risk of convulsions may also increase in patients with epilepsy, those with a history of seizures, or in patients with a recognized risk for seizure (such as head trauma, metabolic disorders, alcohol and drug withdrawal, CNS infections). In tramadol overdose, naloxone administration may increase the risk of seizure.

Serotonin Syndrome Risk

The development of a potentially life-threatening serotonin syndrome may occur with the use of tramadol products, including ULTRACET®, particularly with concomitant use of serotonergic drugs such as SSRIs, SNRIs, TCAs, MAOIs, and triptans, with drugs which impair metabolism of serotonin (including MAOIs), and with drugs which impair metabolism of tramadol (CYP2D6 and CYP3A4 inhibitors). This may occur within the recommended dose (see CLINICAL PHARMACOLOGY, Pharmacokinetics).

Serotonin syndrome may include mental-status changes (e.g., agitation, hallucinations, coma), autonomic instability (e.g., tachycardia, labile blood pressure, hyperthermia), neuromuscular aberrations (e.g., hyperreflexia, incoordination) and/or gastrointestinal symptoms (e.g., nausea, vomiting, diarrhea).

Anaphylactoid Reactions

Serious and rarely fatal anaphylactoid reactions have been reported in patients receiving therapy with tramadol. When these events do occur it is often following the first dose. Other reported allergic reactions include pruritus, hives, bronchospasm, angioedema, toxic epidermal necrolysis and Stevens-Johnson syndrome. Patients with a history of anaphylactoid reactions to codeine and other opioids may be at increased risk and therefore should not receive ULTRACET® (see CONTRAINDICATIONS).

Respiratory Depression

Administer ULTRACET® cautiously in patients at risk for respiratory depression. In these patients, alternative non-opioid analgesics should be considered. When large doses of tramadol are administered with anesthetic medications or alcohol, respiratory depression may result. Respiratory depression should be treated as an overdose. If naloxone is to be administered, use cautiously because it may precipitate seizures (see WARNINGS, Seizure Risk and OVERDOSAGE).

Interaction With Central Nervous System (CNS) Depressants

ULTRACET® should be used with caution and in reduced dosages when administered to patients receiving CNS depressants such as alcohol, opioids, anesthetic agents, narcotics, phenothiazines, tranquilizers or sedative hypnotics. Tramadol increases the risk of CNS and respiratory depression in these patients.

Increased Intracranial Pressure or Head Trauma

ULTRACET® should be used with caution in patients with increased intracranial pressure or head injury. The respiratory depressant effects of opioids include carbon dioxide retention and secondary elevation of cerebrospinal fluid pressure and may be markedly exaggerated in these patients. Additionally, pupillary changes (miosis) from tramadol may obscure the existence, extent, or course of intracranial pathology. Clinicians should also maintain a high index of suspicion for adverse drug reaction when evaluating altered mental status in these patients if they are receiving ULTRACET (see WARNINGS, Respiratory Depression).

Use in Ambulatory Patients

Tramadol may impair the mental and or physical abilities required for the performance of potentially hazardous tasks such as driving a car or operating machinery. The patient using this drug should be cautioned accordingly.

Use With MAO Inhibitors and Serotonin Re-uptake Inhibitors

Use ULTRACET® with great caution in patients taking monoamine oxidase inhibitors. Animal studies have shown increased deaths with combined administration of MAO inhibitors and tramadol. Concomitant use of tramadol with MAO inhibitors or SSRI's increases the risk of adverse events, including seizure and serotonin syndrome.

Use With Alcohol

ULTRACET® should not be used concomitantly with alcohol consumption. The use of ULTRACET® in patients with liver disease is not recommended.

Use With Other Acetaminophen-containing Products

Due to the potential for acetaminophen hepatotoxicity at doses higher than the recommended dose, ULTRACET® should not be used concomitantly with other acetaminophen-containing products.

Withdrawal

Withdrawal symptoms may occur if ULTRACET® is discontinued abruptly (see DRUG ABUSE AND DEPENDENCE). These symptoms may include: anxiety, sweating, insomnia, rigors, pain, nausea, tremors, diarrhea, upper respiratory symptoms, piloerection, and rarely hallucinations. Other symptoms that have been seen less frequently with ULTRACET® discontinuation include: panic attacks, severe anxiety, and paresthesias. Clinical experience suggests that withdrawal symptoms may be avoided by tapering ULTRACET® at the time of discontinuation.

Physical Dependence and Abuse

Tramadol may induce psychic and physical dependence of the morphine-type (µ-opioid) (see DRUG ABUSE AND DEPENDENCE). Tramadol should not be used in opioid-dependent patients. Tramadol has been shown to reinitiate physical dependence in some patients that have been previously dependent on other opioids. Dependence and abuse, including drug-seeking behavior and taking illicit actions to obtain the drug are not limited to those patients with prior history of opioid dependence.

Risk of Overdosage

Serious potential consequences of overdosage with tramadol are central nervous system depression, respiratory depression and death. In treating an overdose, primary attention should be given to maintaining adequate ventilation along with general supportive treatment (see OVERDOSAGE).

Serious potential consequences of overdosage with acetaminophen are hepatic (centrilobular) necrosis, leading to hepatic failure and death. Emergency help should be sought immediately and treatment initiated immediately if overdose is suspected, even if symptoms are not apparent.

PRECAUTIONS

General

The recommended dose of ULTRACET® should not be exceeded.

Do not co-administer ULTRACET® with other tramadol or acetaminophen-containing products (see WARNINGS, Use With Other Acetaminophen-containing Products and Risk of Overdosage).

Pediatric Use

The safety and effectiveness of ULTRACET® has not been studied in the pediatric population.

Geriatric Use

In general, dose selection for an elderly patient should be cautious, reflecting the greater frequency of decreased hepatic, renal, or cardiac function; of concomitant disease and multiple drug therapy.

Acute Abdominal Conditions

The administration of ULTRACET® may complicate the clinical assessment of patients with acute abdominal conditions.

Use in Renal Disease

ULTRACET® has not been studied in patients with impaired renal function. Experience with tramadol suggests that impaired renal function results in a decreased rate and extent of excretion of tramadol and its active metabolite, M1. In patients with creatinine clearances of less than 30 mL/min, it is recommended that the dosing interval of ULTRACET® be increased not to exceed 2 tablets every 12 hours.

Use in Hepatic Disease

ULTRACET® has not been studied in patients with impaired hepatic function. The use of ULTRACET® in patients with hepatic impairment is not recommended (see WARNINGS, Use With Alcohol).

Information for Patients

- Patients should be informed that ULTRACET® may cause seizures and/or serotonin syndrome with concomitant use of serotonergic agents (including SSRIs, SNRIs, and triptans) or drugs that significantly reduce the metabolic clearance of tramadol.
- ULTRACET® may impair mental or physical abilities required for the performance of potentially hazardous tasks such as driving a car or operating machinery.
- ULTRACET® should not be taken with alcohol containing beverages.
- The patient should be instructed not to take ULTRACET® in combination with other tramadol or acetaminophen-containing products, including over-the-counter preparations.
- ULTRACET® should be used with caution when taking medications such as tranquilizers, hypnotics or other opiate containing analgesics.
- The patient should be instructed to inform the physician if they are pregnant, think they might become pregnant, or are trying to become pregnant (see PRECAUTIONS, Labor and Delivery).
- The patient should understand the single-dose and 24-hour dose limit and the time interval between doses, since exceeding these recommendations can result in respiratory depression, seizures, hepatic toxicity and death.

Drug Interactions

CYP2D6 and CYP3A4 Inhibitors

Concomitant administration of CYP2D6 and/or CYP3A4 inhibitors (see CLINICAL PHARMACOLOGY, Pharmacokinetics), such as quinidine, fluoxetine, paroxetine and amitriptyline (CYP2D6 inhibitors), and ketoconazole and erythromycin (CYP3A4 inhibitors), may reduce metabolic clearance of tramadol increasing the risk for serious adverse events including seizures and serotonin syndrome.

Serotonergic Drugs

There have been postmarketing reports of serotonin syndrome with use of tramadol and SSRIs/SNRIs or MAOIs and α2-adrenergic blockers. Caution is advised when ULTRACET® is coadministered with other drugs that may affect the serotonergic neurotransmitter systems, such as SSRIs, MAOIs, triptans, linezolid (an antibiotic which is a reversible non-selective MAOI), lithium, or St. John’s Wort. If concomitant treatment of ULTRACET® with a drug affecting the serotonergic neurotransmitter system is clinically warranted, careful observation of the patient is advised, particularly during treatment initiation and dose increases (see WARNINGS, Serotonin Syndrome).

Triptans

Based on the mechanism of action of tramadol and the potential for serotonin syndrome, caution is advised when ULTRACET® is coadministered with a triptan. If concomitant treatment of ULTRACET® with a triptan is clinically warranted, careful observation of the patient is advised, particularly during treatment initiation and dose increases (see WARNINGS, Serotonin Syndrome).

Use With Carbamazepine

Patients taking carbamazepine may have a significantly reduced analgesic effect of tramadol. Because carbamazepine increases tramadol metabolism and because of the seizure risk associated with tramadol, concomitant administration of ULTRACET® and carbamazepine is not recommended.

Use With Quinidine

Tramadol is metabolized to M1 by CYP2D6. Quinidine is a selective inhibitor of that isoenzyme; so that concomitant administration of quinidine and tramadol results in increased concentrations of tramadol and reduced concentrations of M1. The clinical consequences of these findings are unknown. In vitro drug interaction studies in human liver microsomes indicate that tramadol has no effect on quinidine metabolism.

Potential for Other Drugs to Affect Tramadol

In vitro drug interaction studies in human liver microsomes indicate that concomitant administration with inhibitors of CYP2D6 such as fluoxetine, paroxetine, and amitriptyline could result in some inhibition of the metabolism of tramadol.

Potential for Tramadol to Affect Other Drugs

In vitro studies indicate that tramadol is unlikely to inhibit the CYP3A4-mediated metabolism of other drugs when tramadol is administered concomitantly at therapeutic doses. Tramadol does not appear to induce its own metabolism in humans, since observed maximal plasma concentrations after multiple oral doses are higher than expected based on single-dose data. Tramadol is a mild inducer of selected drug metabolism pathways measured in animals.

Use With Cimetidine

Concomitant administration of ULTRACET® and cimetidine has not been studied. Concomitant administration of tramadol and cimetidine does not result in clinically significant changes in tramadol pharmacokinetics. Therefore, no alteration of the ULTRACET® dosage regimen is recommended.

Use With Digoxin

Post-marketing surveillance of tramadol has revealed rare reports of digoxin toxicity.

Use With Warfarin Like Compounds

Post-marketing surveillance of both tramadol and acetaminophen individual products have revealed rare alterations of warfarin effect, including elevation of prothrombin times.

While such changes have been generally of limited clinical significance for the individual products, periodic evaluation of prothrombin time should be performed when ULTRACET® and warfarin-like compounds are administered concurrently.

Carcinogenesis, Mutagenesis, Impairment of Fertility

There are no animal or laboratory studies on the combination product (tramadol and acetaminophen) to evaluate carcinogenesis, mutagenesis, or impairment of fertility.

A slight but statistically significant increase in two common murine tumors, pulmonary and hepatic, was observed in a mouse carcinogenicity study, particularly in aged mice. Mice were dosed orally up to 30 mg/kg (90 mg/m^2 or 0.5 times the maximum daily human tramadol dosage of 185 mg/m^2) for approximately two years, although the study was not done with the Maximum Tolerated Dose. This finding is not believed to suggest risk in humans. No such finding occurred in rat carcinogenicity study (dosing orally up to 30 mg/kg, 180 mg/m^2, or 1 time the maximum daily human tramadol dosage).

Tramadol was not mutagenic in the following assays: Ames Salmonella microsomal activation test, CHO/HPRT mammalian cell assay, mouse lymphoma assay (in the absence of metabolic activation), dominant lethal mutation tests in mice, chromosome aberration test in Chinese hamsters, and bone marrow micronucleus tests in mice and Chinese hamsters. Weakly mutagenic results occurred in the presence of metabolic activation in the mouse lymphoma assay and micronucleus test in rats. Overall, the weight of evidence from these tests indicates that tramadol does not pose a genotoxic risk to humans.

No effects on fertility were observed for tramadol at oral dose levels up to 50 mg/kg (350 mg/m^2) in male rats and 75 mg/kg (450 mg/m^2) in female rats. These dosages are 1.6 and 2.4 times the maximum daily human tramadol dosage of 185 mg/m^2.

Pregnancy

Teratogenic Effects: Pregnancy Category C

No drug-related teratogenic effects were observed in the progeny of rats treated orally with tramadol and acetaminophen. The tramadol/acetaminophen combination product was shown to be embryotoxic and fetotoxic in rats at a maternally toxic dose, 50/434 mg/kg tramadol/acetaminophen (300/2604 mg/m^2 or 1.6 times the maximum daily human tramadol/acetaminophen dosage of 185/1591 mg/m^2), but was not teratogenic at this dose level. Embryo and fetal toxicity consisted of decreased fetal weights and increased supernumerary ribs.

Non-teratogenic Effects:

Tramadol alone was evaluated in peri- and post-natal studies in rats. Progeny of dams receiving oral (gavage) dose levels of 50 mg/kg (300 mg/m^2 or 1.6 times the maximum daily human tramadol dosage) or greater had decreased weights, and pup survival was decreased early in lactation at 80 mg/kg (480 mg/m^2 or 2.6 times the maximum daily human tramadol dosage).

There are no adequate and well-controlled studies in pregnant women. ULTRACET® should be used during pregnancy only if the potential benefit justifies the potential risk to the fetus. Neonatal seizures, neonatal withdrawal syndrome, fetal death and still birth have been reported with tramadol hydrochloride during post-marketing.

Labor and Delivery

ULTRACET® should not be used in pregnant women prior to or during labor unless the potential benefits outweigh the risks. Safe use in pregnancy has not been established. Chronic use during pregnancy may lead to physical dependence and post-partum withdrawal symptoms in the newborn (see DRUG ABUSE AND DEPENDENCE). Tramadol has been shown to cross the placenta. The mean ratio of serum tramadol in the umbilical veins compared to maternal veins was 0.83 for 40 women given tramadol during labor.

The effect of ULTRACET®, if any, on the later growth, development, and functional maturation of the child is unknown.

Nursing Mothers

ULTRACET® is not recommended for obstetrical preoperative medication or for post-delivery analgesia in nursing mothers because its safety in infants and newborns has not been studied.

Following a single IV 100 mg dose of tramadol, the cumulative excretion in breast milk within 16 hours post-dose was 100 µg of tramadol (0.1% of the maternal dose) and 27 µg of M1.

ADVERSE REACTIONS

Table 2 reports the incidence rate of treatment-emergent adverse events over five days of ULTRACET® use in clinical trials (subjects took an average of at least 6 tablets per day).

Table 2: Incidence of Treatment-Emergent Adverse Events (≥2.0%)
Body System | ULTRACET (N=142)
Preferred Term | (%)
Gastrointestinal System Disorders
Constipation | 6
Diarrhea | 3
Nausea | 3
Dry Mouth | 2
Psychiatric Disorders
Somnolence | 6
Anorexia | 3
Insomnia | 2
Central & Peripheral Nervous System
Dizziness | 3
Skin and Appendages
Sweating Increased | 4
Pruritus | 2
Reproductive Disorders, Male [Number of males = 62]
Prostatic Disorder | 2

Incidence at least 1%, causal relationship at least possible or greater: the following lists adverse reactions that occurred with an incidence of at least 1% in single-dose or repeated-dose clinical trials of ULTRACET®.

Body as a Whole – Asthenia, fatigue, hot flushes

Central and Peripheral Nervous System – Dizziness, headache, tremor

Gastrointestinal System – Abdominal pain, constipation, diarrhea, dyspepsia, flatulence, dry mouth, nausea, vomiting

Psychiatric Disorders – Anorexia, anxiety, confusion, euphoria, insomnia, nervousness, somnolence

Skin and Appendages – Pruritus, rash, increased sweating.

Selected Adverse events occurring at less than 1%: the following lists clinically relevant adverse reactions that occurred with an incidence of less than 1% in ULTRACET® clinical trials.

Body as a Whole – Chest pain, rigors, syncope, withdrawal syndrome

Cardiovascular Disorders– Hypertension, aggravated hypertension, hypotension

Central and Peripheral Nervous System – Ataxia, convulsions, hypertonia, migraine, aggravated migraine, involuntary muscle contractions, paresthesias, stupor, vertigo

Gastrointestinal System– Dysphagia, melena, tongue edema

Hearing and Vestibular Disorders – Tinnitus

Heart Rate and Rhythm Disorders – Arrhythmia, palpitation, tachycardia

Liver and Biliary System– Hepatic function abnormal

Metabolic and Nutritional Disorders – Weight decrease

Psychiatric Disorders – Amnesia, depersonalization, depression, drug abuse, emotional lability, hallucination, impotence, paroniria, abnormal thinking

Red Blood Cell Disorders – Anemia

Respiratory System – Dyspnea

Urinary System – Albuminuria, micturition disorder, oliguria, urinary retention

Vision Disorders – Abnormal vision

Other clinically significant adverse experiences previously reported with tramadol hydrochloride.

Other events which have been reported with the use of tramadol products and for which a causal association has not been determined include: vasodilation, orthostatic hypotension, myocardial ischemia, pulmonary edema, allergic reactions (including anaphylaxis and urticaria, Stevens-Johnson syndrome/TENS), cognitive dysfunction, difficulty concentrating, depression, suicidal tendency, hepatitis liver failure and gastrointestinal bleeding. Reported laboratory abnormalities included elevated creatinine and liver function tests. Serotonin syndrome (whose symptoms may include mental status change, hyperreflexia, fever, shivering, tremor, agitation, diaphoresis, seizures and coma) has been reported with tramadol when used concomitantly with other serotonergic agents such as SSRIs and MAOIs.

Other clinically significant adverse experiences previously reported with acetaminophen.

Allergic reactions (primarily skin rash) or reports of hypersensitivity secondary to acetaminophen are rare and generally controlled by discontinuation of the drug and, when necessary, symptomatic treatment.

DRUG ABUSE AND DEPENDENCE

Tramadol may induce psychic and physical dependence of the morphine-type (µ-opioid) (see WARNINGS). Dependence and abuse, including drug-seeking behavior and taking illicit actions to obtain the drug are not limited to those patients with a prior history of opioid dependence. The risk in patients with substance abuse has been observed to be higher. Tramadol is associated with craving and tolerance development. Withdrawal symptoms may occur if tramadol is discontinued abruptly. These symptoms may include: anxiety, sweating, insomnia, rigors, pain, nausea, tremors, diarrhea, upper respiratory symptoms, piloerection and rarely hallucinations. Other symptoms that have been seen less frequently with ULTRACET® discontinuation include: panic attacks, severe anxiety, and paresthesias. Clinical experience suggests that withdrawal symptoms may be relieved by reinstitution of opioid therapy followed by a gradual, tapered dose reduction of the medication combined with symptomatic support.

OVERDOSAGE

ULTRACET® is a combination product. The clinical presentation of overdose may include the signs and symptoms of tramadol toxicity, acetaminophen toxicity or both. The initial symptoms of tramadol overdosage may include respiratory depression and or seizures. The initial symptoms seen within the first 24 hours following an acetaminophen overdose are: anorexia, nausea, vomiting, malaise, pallor and diaphoresis.

Tramadol

Serious potential consequences of overdosage are respiratory depression, lethargy, coma, seizure, cardiac arrest and death (see WARNINGS). Fatalities have been reported in post marketing in association with both intentional and unintentional overdose with tramadol.

Acetaminophen

Serious potential consequences of overdosage with acetaminophen are hepatic centrilobular necrosis, leading to hepatic failure and death. Renal tubular necrosis, hypoglycemia and coagulation defects also may occur. Early symptoms following a potentially hepatotoxic overdose may include: nausea, vomiting, diaphoresis and general malaise. Clinical and laboratory evidence of hepatic toxicity may not be apparent until 48 to 72 hours post ingestion.

TREATMENT OF OVERDOSE

A single or multiple overdose with ULTRACET® may be a potentially lethal polydrug overdose, and consultation with a regional poison control center is recommended.

In treating an overdose of ULTRACET®, primary attention should be given to maintaining adequate ventilation along with general supportive treatment. While naloxone will reverse some, but not all, symptoms caused by overdosage with tramadol, the risk of seizures is also increased with naloxone administration. In animals, convulsions following the administration of toxic doses of tramadol could be suppressed with barbiturates or benzodiazepines but were increased with naloxone. Naloxone administration did not change the lethality of an overdose in mice. Based on experience with tramadol, hemodialysis is not expected to be helpful in an overdose because it removes less than 7% of the administered dose in a 4-hour dialysis period.

Standard recommendations should be followed for the treatment of acetaminophen overdose.

DOSAGE AND ADMINISTRATION

For the short-term (five days or less) management of acute pain, the recommended dose of ULTRACET® is 2 tablets every 4 to 6 hours as needed for pain relief up to a maximum of 8 tablets per day.

Individualization of Dose

In patients with creatinine clearances of less than 30 mL/min, it is recommended that the dosing interval of ULTRACET® be increased not to exceed 2 tablets every 12 hours. Dose selection for an elderly patient should be cautious, in view of the potential for greater sensitivity to adverse events.

HOW SUPPLIED

ULTRACET® (tramadol hydrochloride/acetaminophen) Tablets with tramadol 37.5 mg and acetaminophen 325 mg are light yellow, coated, capsule-shaped tablets imprinted "O-M" on one side and "650" on the other are available as follows:

120's: | NDC 21695-143-72 | Bottles of 120 tablets

Dispense in a tight container. Store at 25°C (77°F); excursions permitted to 15 – 30°C (59 – 86°F).

Manufactured by:
Janssen Ortho, LLC
Gurabo, Puerto Rico 00778

Distributed by:
OMP DIVISION
ORTHO-McNEIL PHARMACEUTICAL, INC.
Raritan, New Jersey 08869

Repackaged by:

REBEL DISTRIBUTORS CORP

Thousand Oaks, CA 91320